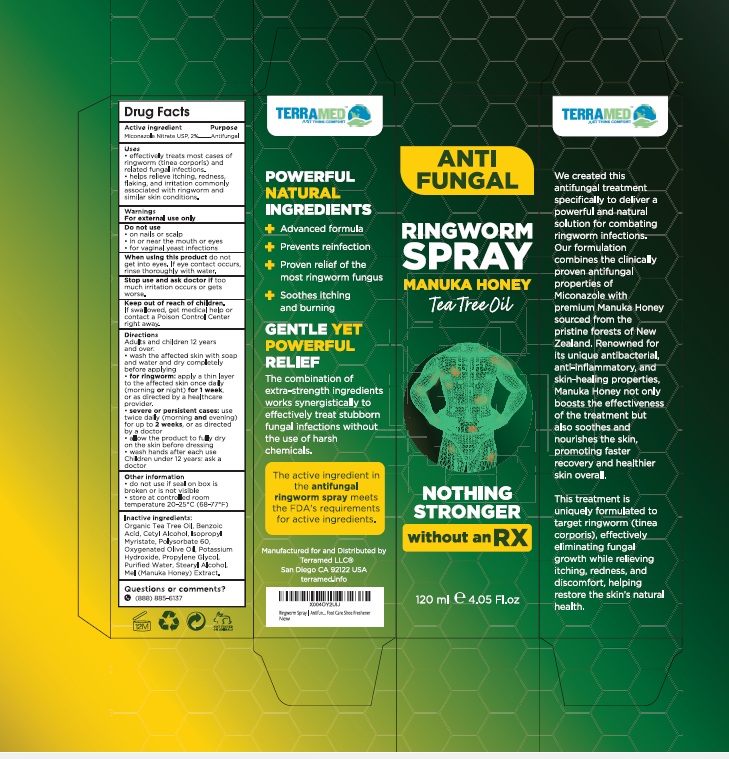 DRUG LABEL: Antifungal Ringworm Treatment
NDC: 83004-030 | Form: SPRAY
Manufacturer: Rida LLC
Category: otc | Type: HUMAN OTC DRUG LABEL
Date: 20260115

ACTIVE INGREDIENTS: MICONAZOLE NITRATE 2 g/100 mL
INACTIVE INGREDIENTS: WATER; PROPYLENE GLYCOL; STEARYL ALCOHOL; DIMETHICONE, UNSPECIFIED; ISOPROPYL ALCOHOL; SODIUM LAURYL SULFATE; BENZYL ALCOHOL; HYDROXYETHYL CELLULOSE, UNSPECIFIED; ETHYLPARABEN; PROPYLPARABEN; SODIUM CHLORIDE

Active Ingredient

Miconazole Nitrate 2%

Purpose

Anti-fungal

Uses

- effectively treats most of cases of ringworm (tinea corporis) and related fungal infections.
- helps relieve itching, redness, flaking, and irritation commonly associated with ringworm and similar skin conditions.

Directions

Adults and children 12 years and over

- Wash the affected skin with soap and water and dry completely before applying.
- for ringworm: apply a thin layer to the affected skin once daily (morning or night) for 1 week, or as directed by a doctor
- severe or persistent cases: use twice daily (morning and evening) for up to 2 weeks, or as directed by a doctor
- allow the product to fully dry on the skin before dressing
- wash hands after each use children under 12 years: ask a doctor.

Warnings

- For external use only

Do not use

- on nails or scalp
- in or near the mouth or eyes
- for vaginal yeast infections

When using this product

. Do not get into the eyes. If eye contact occurs, rinse thoroughly with water.

Stop use and ask a doctor

if too much irritation occurs or gets worse.

Keep out of reach of children. If swallowed, get medical help or contact a Poison Control Center right away.

Other Information

- do not use if seal on box is brken or is not visible
- store at controlled room temperature 20-25°C (68-77°F)

Inactive ingredients

Organic tea tree oil, Benzoic acid, Cetyl alcohol, Isopropyl Myristate, Polysorbate 60, Oxygenated olive oil, Potassium hydroxide, Propylene glycol, Purified water, Stearyl alcohol, Mel (Manuka Honey) Extract.